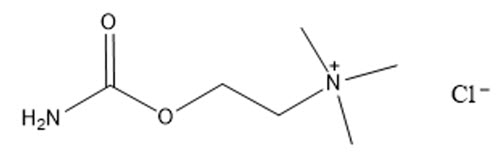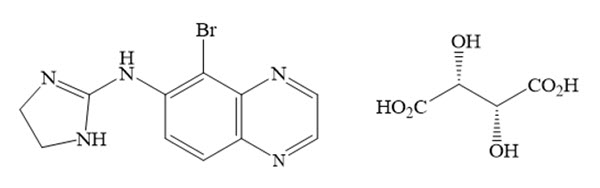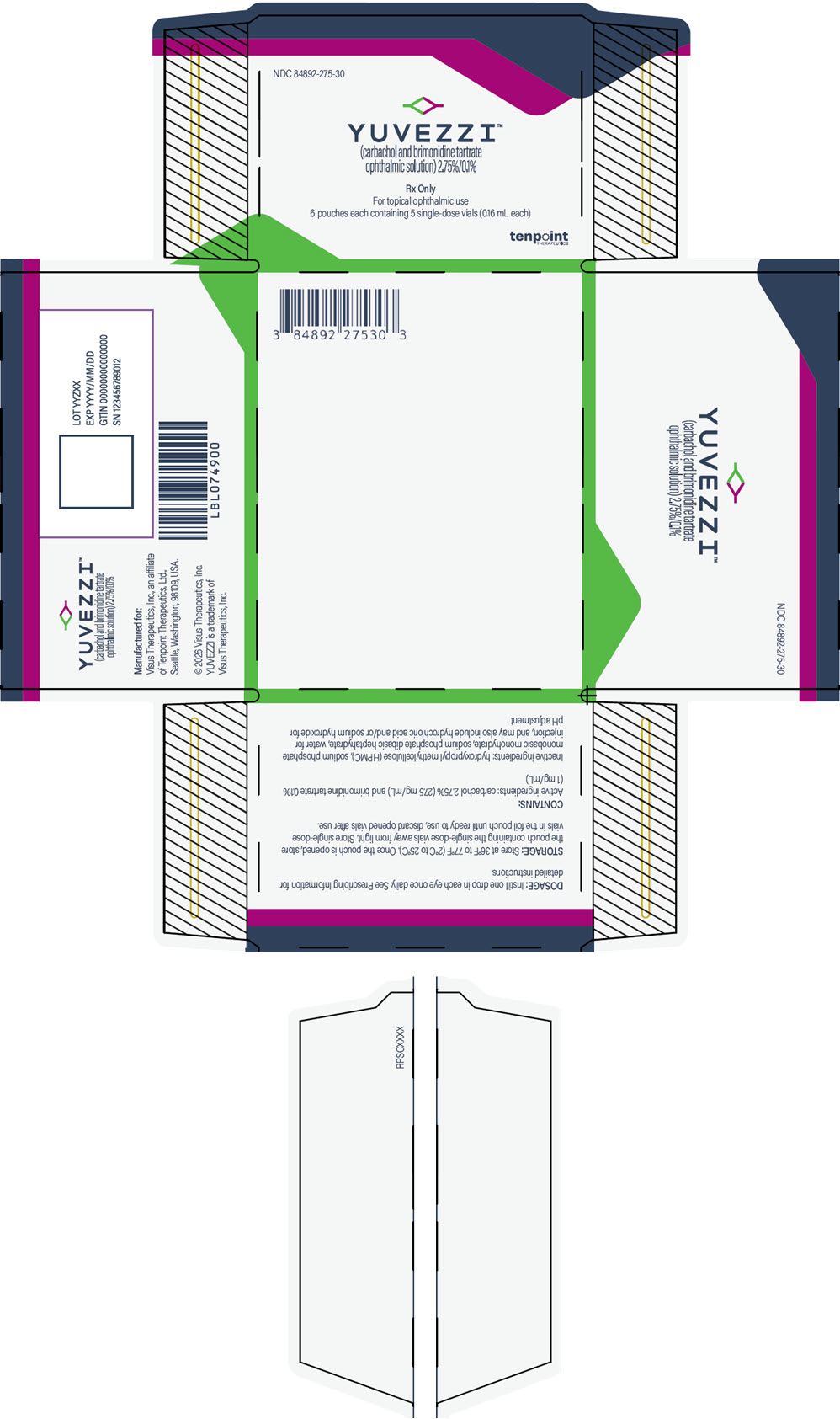 DRUG LABEL: YUVEZZI
NDC: 84892-275 | Form: SOLUTION/ DROPS
Manufacturer: Visus Therapeutics, Inc.
Category: prescription | Type: HUMAN PRESCRIPTION DRUG LABEL
Date: 20260219

ACTIVE INGREDIENTS: CARBACHOL 27.5 mg/1 mL; BRIMONIDINE TARTRATE 1 mg/1 mL
INACTIVE INGREDIENTS: HYPROMELLOSE, UNSPECIFIED; SODIUM PHOSPHATE, MONOBASIC, MONOHYDRATE; SODIUM PHOSPHATE, DIBASIC, HEPTAHYDRATE; WATER; HYDROCHLORIC ACID; SODIUM HYDROXIDE

HIGHLIGHTS OF PRESCRIBING INFORMATION

These highlights do not include all the information needed to use YUVEZZI™ safely and effectively. See full prescribing information for YUVEZZI.
YUVEZZI (carbachol and brimonidine tartrate ophthalmic solution) 2.75% / 0.1%, for topical ophthalmic use
Initial U.S. Approval: 2026

1 INDICATIONS AND USAGE

YUVEZZI is a combination of carbachol, a cholinergic agonist, and brimonidine, an alpha-adrenergic receptor agonist, indicated for the treatment of presbyopia in adults. (1)

2 DOSAGE AND ADMINISTRATION

Instill one drop in each eye once daily. (2.1)

3 DOSAGE FORMS AND STRENGTHS

Ophthalmic solution: carbachol 2.75% and brimonidine tartrate 0.1% in a single-dose vial. (3)

4 CONTRAINDICATIONS

Hypersensitivity. (4)

5 WARNINGS AND PRECAUTIONS

- Blurred Vision: Advise patients not to drive or operate machinery if vision is not clear (e.g., blurred vision). Exercise caution in night driving and other hazardous activities in poor illumination. (5.1)
- Risk of Retinal Detachment: Rare cases of retinal tear and detachment have been reported with miotics. Individuals with preexisting retinal disease are at increased risk. Therefore, examination of the retina is advised in all patients prior to initiation of therapy. Patients should be advised to seek immediate medical care with sudden onset of flashes of lights, floaters, or vision loss. (5.2)
- Iritis: Caution is advised in patients with iritis. (5.3)
- Potentiation of Vascular Insufficiency: Use with caution in patients with depression, cerebral or coronary insufficiency, Raynaud's phenomenon, orthostatic hypotension, or thromboangiitis obliterans. (5.4)

6 ADVERSE REACTIONS

Most common adverse reactions (incidence >5%) are eye pain upon instillation, visual impairment, eye irritation upon instillation, and headache. (6.1)

To report SUSPECTED ADVERSE REACTIONS, contact Visus Therapeutics, Inc., at 1-888-735-0821 or FDA at 1-800-FDA-1088 or www.fda.gov/medwatch.

7 DRUG INTERACTIONS

Antihypertensives/cardiac glycosides may lower blood pressure. (7.1)

Use with CNS depressants may result in an additive or potentiating effect. (7.2)

Tricyclic antidepressants may potentially blunt the hypotensive effect of systemic clonidine. (7.3)

Monoamine oxidase inhibitors may result in increased hypotension. (7.4)

FULL PRESCRIBING INFORMATION

1 INDICATIONS AND USAGE

YUVEZZI™ is indicated for the treatment of presbyopia in adults.

2 DOSAGE AND ADMINISTRATION

2.1 Recommended Dosage

The recommended dosage of YUVEZZI is one drop in each eye once daily.

2.2 Administration Instructions

Remove contact lenses prior to instillation of YUVEZZI. Wait 10 minutes after dosing before reinserting contact lenses.

If more than one topical ophthalmic medication is being used, the medicines must be administered at least 5 minutes apart.

One single-dose vial can be used to dose both eyes. Discard the open single-dose vial and any remaining contents immediately after use.

3 DOSAGE FORMS AND STRENGTHS

Ophthalmic solution: carbachol 2.75% (27.5 mg/mL) and brimonidine tartrate 0.1% (1 mg/mL) as a clear, greenish-yellow ophthalmic solution in single-dose vials.

4 CONTRAINDICATIONS

YUVEZZI is contraindicated in patients with known hypersensitivity to the active ingredients or to any of the excipients.

5 WARNINGS AND PRECAUTIONS

5.1 Blurred Vision

Miotics may cause accommodative spasm. Advise patients to not drive or operate machinery if vision is not clear (e.g., blurred vision).

In addition, patients may experience temporary dim or dark vision with miotics. Advise patients to exercise caution in night driving and other hazardous activities in poor illumination.

5.2 Risk of Retinal Detachment

Rare cases of retinal tear and detachment have been reported with miotics. Individuals with pre-existing retinal disease are at increased risk. Examination of the retina is advised in all patients prior to the initiation of therapy.

Advise patients to seek immediate medical care with sudden onset of flashes of lights, floaters, or vision loss.

5.3 Iritis

Sequelae of ocular inflammation, i.e., adhesions (synechiae) between the iris and the lens, may be exacerbated with miotic use, therefore, YUVEZZI is not recommended to be used when iritis is present.

5.4 Potentiation of Vascular Insufficiency

YUVEZZI may potentiate syndromes associated with vascular insufficiency. YUVEZZI should be used with caution in patients with depression, cerebral or coronary insufficiency, Raynaud's phenomenon, orthostatic hypotension, or thromboangiitis obliterans.

5.5 Potential for Eye Injury or Contamination

To prevent eye injury or contamination, avoid touching the single-dose vial to the eye, eyelids, or to any other surface.

6 ADVERSE REACTIONS

The following clinically significant adverse reactions are described elsewhere in labeling:

- Hypersensitivity [see Contraindications (4)]

6.1 Clinical Trials Experience

Because clinical trials are conducted under widely varying conditions, adverse reaction rates observed in the clinical trials of a drug cannot be directly compared to rates in the clinical trials of another drug and may not reflect the rates observed in practice.

YUVEZZI was evaluated in 536 patients with presbyopia in two randomized, double-masked, controlled studies. BRIO™ I (NCT05270863) was a single-dose crossover study in which 178 patients received YUVEZZI. BRIO II (NCT05135286) included 358 patients who received YUVEZZI in the long-term safety portion of the study (up to 12 months duration, including a 6-month open-label extension). Adverse reactions reported in > 5% to 7% of participants were eye pain upon instillation and visual impairment. Adverse reactions reported in > 10% to 16% of participants were eye irritation upon instillation and headache. The majority of adverse events were mild, transient, and self-resolving.

7 DRUG INTERACTIONS

7.1 Antihypertensives/Cardiac Glycosides

Because brimonidine tartrate, a component of YUVEZZI, may reduce blood pressure, caution in using drugs such as antihypertensives and/or cardiac glycosides with YUVEZZI is advised.

7.2 CNS Depressants

Although specific drug interaction studies have not been conducted with YUVEZZI, the possibility of an additive or potentiating effect with central nervous system (CNS) depressants (alcohol, opiates, barbiturates, sedatives, or anesthetics) should be considered.

7.3 Tricyclic Antidepressants

Tricyclic antidepressants have been reported to blunt the hypotensive effect of systemic clonidine. It is not known whether the concurrent use of these agents with YUVEZZI in humans can lead to resulting interference with pupil constriction effects. Caution is advised in patients taking tricyclic antidepressants, which can affect the metabolism and uptake of circulating amines.

7.4 Monoamine Oxidase Inhibitors

Monoamine oxidase (MAO) inhibitors may theoretically interfere with the metabolism of brimonidine tartrate and potentially result in an increased systemic side effect such as hypotension. Caution is advised in patients taking MAO inhibitors which can affect the metabolism and uptake of circulating amines.

8 USE IN SPECIFIC POPULATIONS

8.1 Pregnancy

Risk Summary

There are no adequate and well-controlled studies of YUVEZZI administration in pregnant women to inform a drug-associated risk. Topical ocular administration of YUVEZZI to pregnant rats throughout organogenesis did not produce adverse effects up to 3 times the maximum recommended human ocular dose (MRHOD). Topical ocular administration of YUVEZZI to pregnant rabbits throughout organogenesis at approximately 3 times the MRHOD resulted in maternal toxicity with no effect on the fetus, including reduced maternal food consumption, body weight change, and related moribundity in 2/25 animals during the dosing period. Body weight and food consumption effects recovered after the dosing stopped (see Data).

Because animal reproductive studies are not always predictive of human response, YUVEZZI should be administered during pregnancy only if the potential benefit justifies the potential risk to the pregnant mother and fetus. The background risk of major birth defects and miscarriage for the indicated population is unknown. However, the background risk in the U.S. general population of major birth defects is 2 to 4%, and of miscarriage is 15 to 20%, of clinically recognized pregnancies.

Data

Human Data

No adequate and well-controlled trials of YUVEZZI have been conducted in pregnant women.

Animal Data

YUVEZZI was not teratogenic in embryofetal development studies when given by topical ocular administration to pregnant rats or rabbits throughout organogenesis at dose levels up to approximately 3 times the MRHOD of 1.815 mg/day carbachol and 0.066 mg/day brimonidine tartrate based on body surface area scaling. Topical ocular administration of YUVEZZI to pregnant rats on gestation days (GD) 6 to 17 at dose levels of up to 0.224 mg/day carbachol and 0.008 mg/day brimonidine tartrate (approximately 3 times the MRHOD, based on body surface area) produced no maternal toxicity or embryofetal effects. Topical ocular administration of YUVEZZI to pregnant rabbits on GD 7 to 19 at the dose level of 1.12 mg/day carbachol and 0.04 mg/day brimonidine tartrate (approximately 3 times the MRHOD, based on body surface area scaling) led to maternal toxicity with no embryofetal effects. Maternal findings included significantly reduced food consumption (41%) and body weight change (-87%), with related moribundity in 2/25 animals during the dosing period, compared with the vehicle control group. Body weight and food consumption effects resolved after a 10-day recovery period.

8.2 Lactation

Risk Summary

There is no information regarding the presence of carbachol and brimonidine tartrate in human milk, the effects on the breastfed infants, or the effects on milk production to inform risk of YUVEZZI to an infant during lactation.

Systemic levels of carbachol and brimonidine tartrate following topical ocular administration of YUVEZZI are low [see Clinical Pharmacology (12.3)] , and it is not known whether measurable levels of carbachol and brimonidine tartrate would be present in maternal milk following topical ocular administration.

The developmental and health benefits of breastfeeding should be considered along with the mother's clinical need for YUVEZZI and any potential adverse effects on the breastfed child from YUVEZZI.

8.4 Pediatric Use

Presbyopia does not occur in the pediatric population.

8.5 Geriatric Use

No overall differences in safety or effectiveness have been observed between elderly and adult patients.

10 OVERDOSAGE

Systemic toxicity following topical ocular administration of carbachol is rare, but patients who are sensitive may occasionally develop sweating and gastrointestinal overactivity. Accidental ingestion can produce sweating, salivation, nausea, and a decrease in blood pressure. In moderate overdosage, spontaneous recovery is to be expected and is aided by intravenous fluids to compensate for dehydration. For patients demonstrating severe poisoning, use atropine, the pharmacologic antagonist to carbachol.

Very limited information exists on accidental ingestion of brimonidine in adults; the only adverse reaction reported to date has been hypotension. Treatment of an oral overdose includes supportive and symptomatic therapy; a patent airway should be maintained.

11 DESCRIPTION

YUVEZZI (carbachol and brimonidine tartrate ophthalmic solution) 2.75% / 0.1% is a fixed-dose combination of carbachol, a cholinergic agonist, and brimonidine, an alpha-adrenergic receptor agonist, for topical ophthalmic use. YUVEZZI is formulated as an isotonic, sterile, clear, greenish-yellow ophthalmic solution. YUVEZZI does not contain an anti-microbial preservative.

The chemical name for carbachol is 2-carbamoyloxyethyl(trimethyl)azanium chloride. The molecular weight is 182.648 g/mol and the molecular formula is C6H15ClN2O2. Its structural formula is:

The chemical name for brimonidine tartrate is 5-bromo-N-(4,5-dihydro-1H-imidazol-2-yl)-6-quinoxalinamine L-tartrate. The molecular weight is 442.226 g/mol and the molecular formula is C15H16BrN5O6. Its structural formula is:

Each mL of YUVEZZI contains carbachol 2.75% (27.5 mg/mL) and brimonidine tartrate 0.1% (1 mg/mL) as the active ingredients. Inactive ingredients are: hydroxypropyl methylcellulose (HPMC), sodium phosphate monobasic monohydrate, sodium phosphate dibasic heptahydrate, water for injection, and may also include hydrochloric acid and/or sodium hydroxide to adjust pH, if necessary.

12 CLINICAL PHARMACOLOGY

12.1 Mechanism of Action

The proposed mechanism of action of this fixed-dose combination of carbachol and brimonidine in presbyopia is pupillary constriction and the creation of a pinhole effect that improves near visual acuity and depth of focus. Carbachol is a cholinergic agent which produces constriction of the iris sphincter and ciliary body. Brimonidine tartrate, an alpha-adrenergic agonist, blocks contraction of the iris dilator muscle and relaxes tonic contraction of the ciliary muscle, enhancing selectivity for the pupil and increasing bioavailability of carbachol in the aqueous humor.

12.2 Pharmacodynamics

Pupil size was assessed using automated digital pupillometry under mesopic conditions. Average pupil diameter reduction following YUVEZZI was significantly superior to both active monotherapies from pre-dose baseline to Hour 0.5 through Hour 10 in the BRIO I study, and to vehicle from pre-dose baseline to Hour 0.5 through Hour 8 in the BRIO II study.

12.3 Pharmacokinetics

Absorption

Systemic exposures to brimonidine tartrate and carbachol were evaluated in participants with presbyopia who were administered 1 drop of YUVEZZI to each eye. Brimonidine tartrate plasma concentrations were quantifiable in 5 of 14 subjects, with Cmaxand Tmaxup to 0.066 ng/mL and 0.52 hours respectively. Carbachol plasma concentrations were quantifiable in 6 of 14 subjects, with Cmaxand Tmaxup to 1.02 ng/mL and 4.42 hours respectively.

Distribution

Brimonidine is approximately 29% bound to plasma proteins in healthy subjects. The protein binding of carbachol has not been studied.

Elimination

Metabolism

In humans, brimonidine is extensively metabolized by the liver. Metabolism of carbachol has not been studied.

Excretion

Urinary excretion is the major route of elimination of brimonidine and its metabolites. Approximately 87% of an orally administered radioactive dose of brimonidine was eliminated within 120 hours, with 74% found in the urine. Excretion of carbachol has not been studied.

13 NONCLINICAL TOXICOLOGY

13.1 Carcinogenesis, Mutagenesis, Impairment of Fertility

Carcinogenesis

Long term studies in animals have not been performed to evaluate carcinogenic potential of YUVEZZI or carbachol.

No brimonidine tartrate–related carcinogenic effects were observed with dietary administration at dose levels up to 2.5 mg/kg/day in mice for 21 months or 1 mg/kg/day in rats for 24 months.

Mutagenesis

Carbachol was not mutagenic or clastogenic in a battery of in vitro and in vivo studies including the Ames bacterial reverse mutation test, an in vitro micronucleus assay in TK6 cells, and an in vivo rat bone marrow micronucleus assay.

Brimonidine tartrate was not mutagenic or clastogenic in a series of in vitro and in vivo studies, including the Ames bacterial reverse mutation test, a chromosomal aberration assay in Chinese Hamster Ovary (CHO) cells, and 3 in vivo studies in CD-1 mice: a host-mediated assay, cytogenic study, and dominant lethal assay.

Impairment of Fertility

Fertility studies of YUVEZZI or carbachol have not been conducted.

A reproduction and fertility study in rats with brimonidine tartrate demonstrated no adverse effect on male or female fertility at oral doses up to 1 mg/kg.

14 CLINICAL STUDIES

The efficacy of YUVEZZI for the treatment of presbyopia was demonstrated in two Phase 3, randomized, double‐masked, controlled studies in participants 45 to 80 years old with presbyopia. BRIO I was a crossover study in which 182 participants received a single administration of 1 drop of YUVEZZI, carbachol, and brimonidine tartrate in each eye with at least 3 days between treatments and was designed to evaluate the superiority of YUVEZZI over either active monotherapy. In BRIO II, 436 participants were randomized for a single administration of 1 drop of YUVEZZI or vehicle (218 to each group) in each eye. In addition, participants administered 1 drop of YUVEZZI or vehicle once daily for 6 months followed by a 6-month open-label extension. Both studies included participants who were post-refractive surgery and/or pseudophakic.

The proportions of participants achieving a gain from baseline of 3 lines (15 letters) or more in binocular uncorrected near visual acuity (BUCNVA) without a loss of 1 line (5 letters) or more in binocular uncorrected distance visual acuity (BUCDVA) under mesopic conditions were evaluated.

Table 1 demonstrates the effect on presbyopia, from 30 minutes post dose to 8 hours.

Table 1. Proportion of participants from BRIO I and BRIO II studies achieving a gain from baseline of 3 lines (15 letters) or more in BUCNVA without a loss of 1 line (5 letters) or more in BUCDVA
Timepoint | BRIO I |  |  | BRIO II
Timepoint | YUVEZZI (N=182) | Brimonidine tartrate (N=182) | Carbachol (N=182) | YUVEZZI (N=218) | Vehicle (N=218)
Hour 0.5 | 27.0% | 10.8% (p<0.01) | 24.9% (p=0.54) | 19.4% | 1.8% (p<0.01)
Hour 1 | 49.4% | 22.7% (p<0.01) | 35.0% (p<0.01) | 38.2% | 3.7% (p<0.01)
Hour 2 | 51.1% | 26.7% (p<0.01) | 39.8% (p<0.01) | 34.1% | 3.7% (p<0.01)
Hour 4 | 32.0% | 22.2% (p=0.02) | 21.6% (p=0.01) | 20.3% | 2.8% (p<0.01)
Hour 6 | 22.5% | 14.8% (p=0.04) | 13.7% (p<0.01) | 13.8% | 2.8% (p<0.01)
Hour 8 | 13.5% | 12.5% (p=0.73) | 8.6% (p=0.10) | 10.2% | 3.2% (p=0.01)
P-values are for comparisons to YUVEZZI.
Abbreviations: N: number of participants in the study arm.

16 HOW SUPPLIED/STORAGE AND HANDLING

YUVEZZI (carbachol and brimonidine tartrate ophthalmic solution) 2.75% / 0.1% is supplied as a clear, greenish-yellow ophthalmic solution in a low-density polyethylene (LDPE) single-dose vial, as follows:

Carton box of 30 single-dose vials (6 pouches each containing 5 vials) | NDC 84892-275-30

Storage

Store at 36°F to 77°F (2°C to 25°C). Once a pouch is opened, store the single-dose vials in the foil pouch away from light until ready for use. Discard opened single-dose vials and any remaining contents immediately after use.

17 PATIENT COUNSELING INFORMATION

Night Driving

Advise patients that they may experience temporary dim or dark vision. Advise patients to exercise caution with night driving and when hazardous activities are undertaken in poor illumination [see Warnings and Precautions (5.1)] .

Blurred Vision

Temporary problems when changing focus between near objects and distant objects may occur. Advise patients not to drive or use machinery if vision is not clear [see Warnings and Precautions (5.1)] .

When to Seek Physician Advice

Advise patients to seek immediate medical care with sudden onset of flashes of lights, floaters, or vision loss [see Warnings and Precautions (5.2)] .

Contact Lens Wear

Advise patients to remove contact lenses prior to the instillation of YUVEZZI. Wait 10 minutes after dosing before reinserting contact lenses [see Dosage and Administration (2.2)] .

Potential for Eye Injury or Contamination of the Product

Advise patients to avoid touching the tip of the single-dose vial to the eye, eyelids, or to any other surface to prevent eye injury or contamination [see Warnings and Precautions (5.5)] . Advise patients to discard the opened single-dose vial and any remaining contents immediately after use.

Concomitant Topical Ocular Therapy

Advise patients that if more than one topical ophthalmic medication is being used, the medicines must be administered at least 5 minutes apart [see Dosage and Administration (2.2)] .

Manufactured for: Visus Therapeutics, Inc., an affiliate of Tenpoint Therapeutics, Ltd., Seattle, Washington, 98109, USA.

© 2026 Visus Therapeutics, Inc.

YUVEZZI and BRIO are trademarks of Visus Therapeutics, Inc.

Tenpoint is a trademark of Tenpoint Therapeutics Holding Limited.

PRINCIPAL DISPLAY PANEL - 0.16 mL Vial Pouch Carton

NDC 84892-275-30

YUVEZZI™
(carbachol and brimonidine tartrate
ophthalmic solution) 2.75%/0.1%

Rx Only

For topical ophthalmic use

6 pouches each containing 5 single-dose vials (0.16 mL each)

tenpoint
THERAPEUTICS